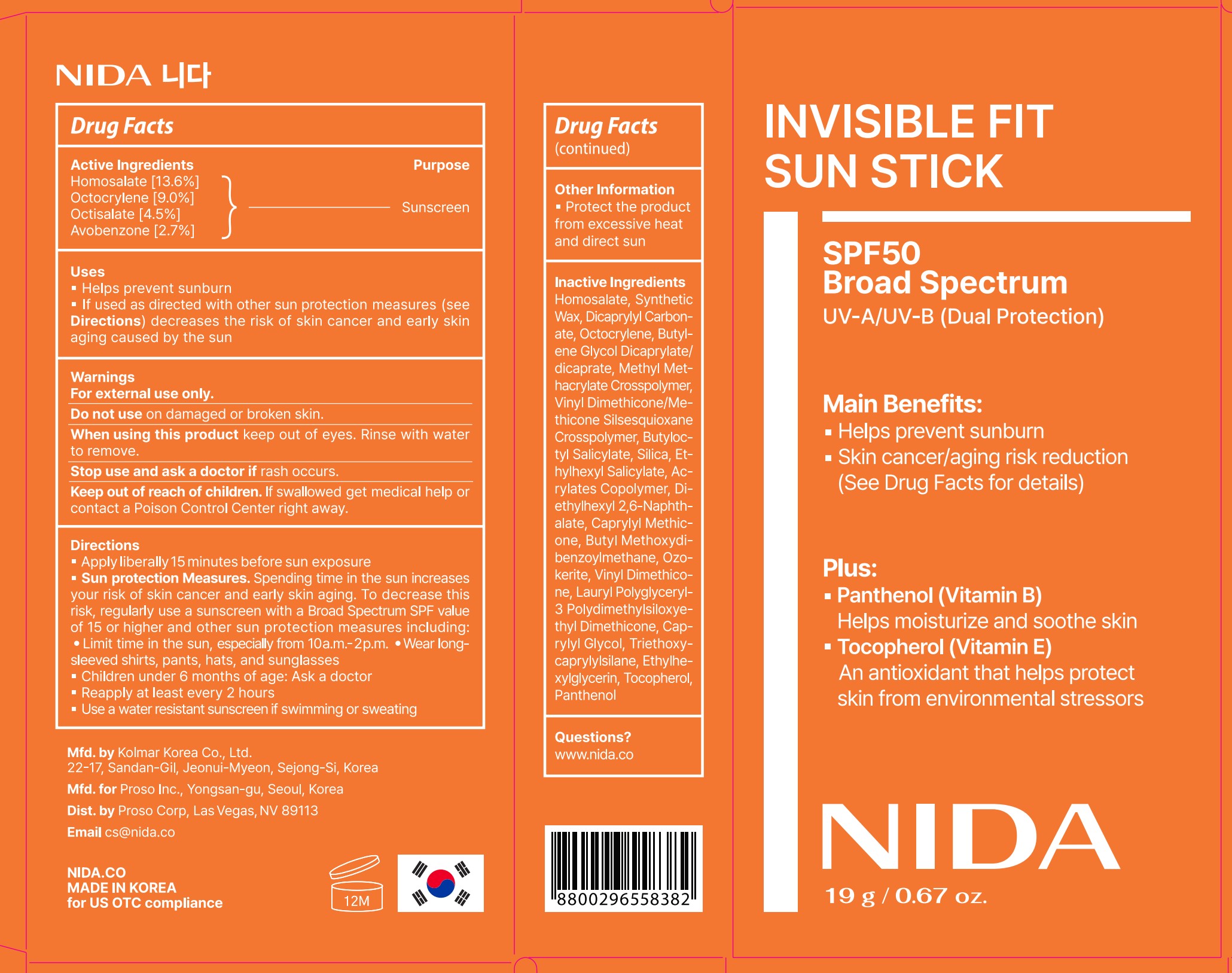 DRUG LABEL: NIDA Invisible Fit Sun Stick
NDC: 87335-002 | Form: STICK
Manufacturer: Proso Corp
Category: otc | Type: HUMAN OTC DRUG LABEL
Date: 20260203

ACTIVE INGREDIENTS: OCTISALATE 45 mg/1 g; OCTOCRYLENE 90 mg/1 g; HOMOSALATE 136 mg/1 g; AVOBENZONE 27 mg/1 g
INACTIVE INGREDIENTS: PANTHENOL; DICAPRYLYL CARBONATE; DIMETHICONE/VINYL DIMETHICONE CROSSPOLYMER (SOFT PARTICLE); SYNTHETIC WAX (540 MW); TOCOPHEROL; VINYL DIMETHICONE/METHICONE SILSESQUIOXANE CROSSPOLYMER; SILICA; BUTYL ACRYLATE/METHYL METHACRYLATE/METHACRYLIC ACID COPOLYMER (18000 MW); BUTYLOCTYL SALICYLATE; CAPRYLYL METHICONE; BUTYLENE GLYCOL DICAPRYLATE/DICAPRATE; METHYL METHACRYLATE/GLYCOL DIMETHACRYLATE CROSSPOLYMER; LAURYL POLYGLYCERYL-3 POLYDIMETHYLSILOXYETHYL DIMETHICONE (4000 MPA.S); CERESIN; TRIETHOXYCAPRYLYLSILANE; ETHYLHEXYLGLYCERIN; DIETHYLHEXYL 2,6-NAPHTHALATE; CAPRYLYL GLYCOL

Directions

Apply liberally 15 minutes before sun exposure

Sun protection Measures. Spending time in the sun increases your risk of skin cancer and early skin aging. To decrease this risk, regularly use a sunscreen with a Broad Spectrum SPF value of 15 or higher and other sun protection measures including: • Limit time in the sun, especially from 10a.m.– 2p.m. • Wear long-sleeved shirts, pants, hats, and sunglasses

Children under 6 months of age: Ask a doctor

Reapply at least every 2 hours

Use a water resistant sunscreen if swimming or sweating

Warnings

For external use only.

Do not use on damaged or broken skin.

When using this product keep out of eyes. Rinse with water to remove.

Stop use and ask a doctor if rash occurs.

Keep out of reach of children. If swallowed get medical help or contact a Poison Control Center right away.

Uses

Helps prevent sunburn

If used as directed with other sun protection measures (see Directions) decreases the risk of skin cancer and early skin aging caused by the sun

Keep out of reach of children. If swallowed get medical help or contact a Poison Control Center right away.

Purpose Sunscreen

Active Ingredients

Homosalate [13.6%]

Octocrylene [9.0%]

Octisalate [4.5%]

Avobenzone [2.7%]

INACTIVE INGREDIENT

SYNTHETIC WAX
DICAPRYLYL CARBONATE
BUTYLENE GLYCOL DICAPRYLATE/DICAPRATE
METHYL METHACRYLATE CROSSPOLYMER
VINYL DIMETHICONE/METHICONE SILSESQUIOXANE CROSSPOLYMER
BUTYLOCTYL SALICYLATE
SILICA
ACRYLATES COPOLYMER
DIETHYLHEXYL 2,6-NAPHTHALATE
CAPRYLYL METHICONE
OZOKERITE
VINYL DIMETHICONE
LAURYL POLYGLYCERYL-3 POLYDIMETHYLSILOXYETHYL DIMETHICONE
CAPRYLYL GLYCOL
TRIETHOXYCAPRYLYLSILANE
ETHYLHEXYLGLYCERIN
TOCOPHEROL
PANTHENOL